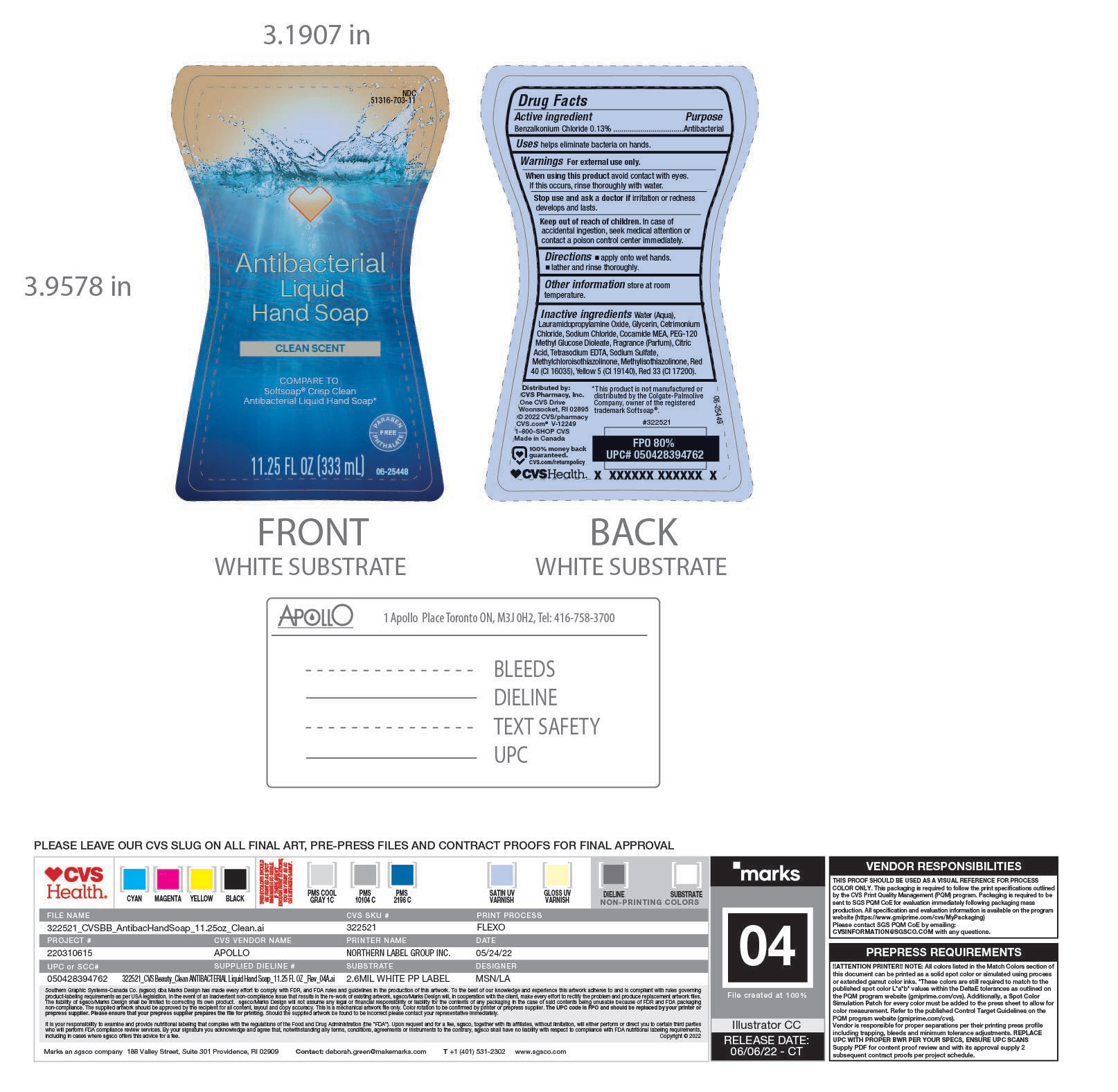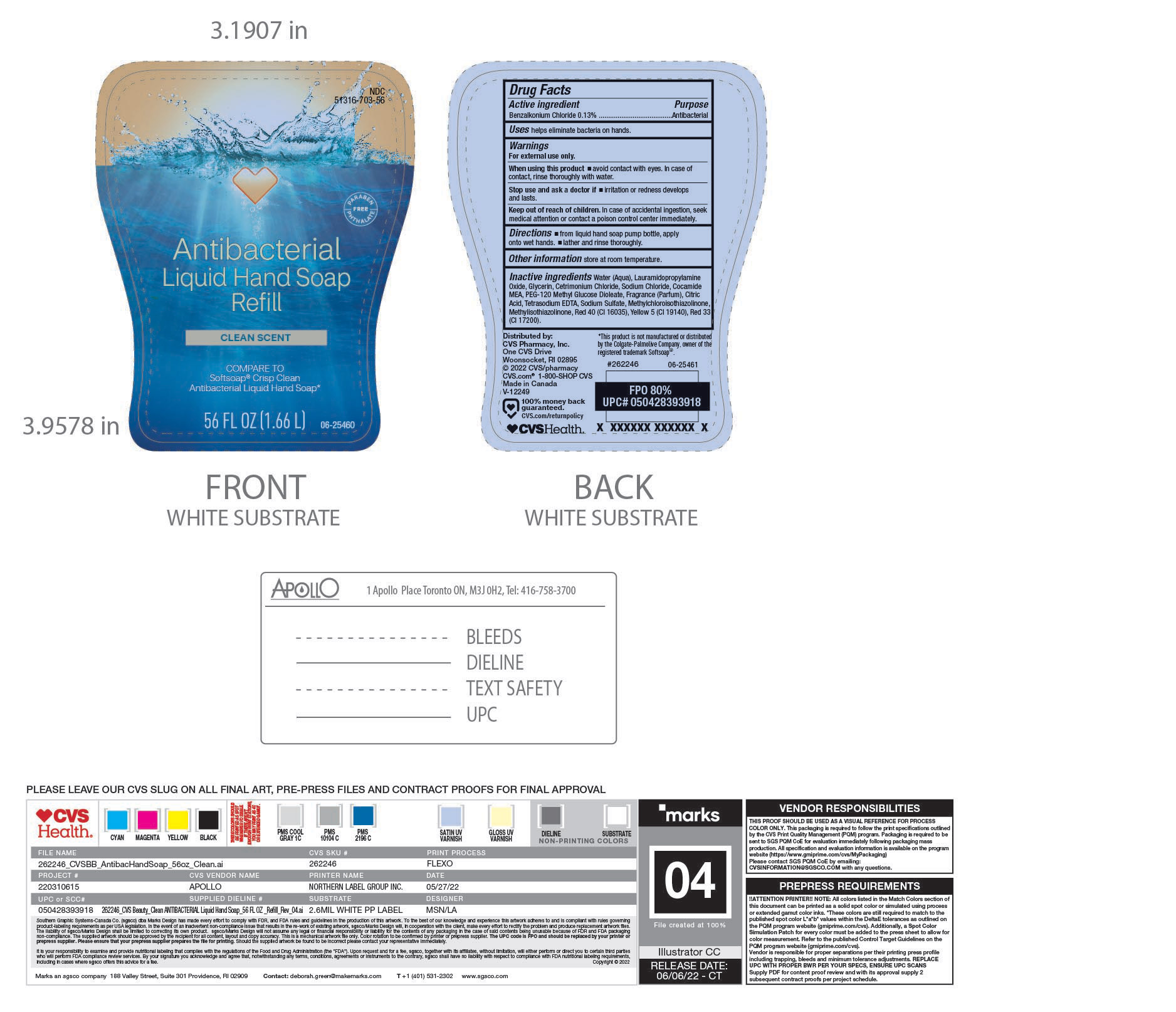 DRUG LABEL: Handsoap
NDC: 51316-703 | Form: SOAP
Manufacturer: CVS Pharmacy
Category: otc | Type: HUMAN OTC DRUG LABEL
Date: 20250206

ACTIVE INGREDIENTS: BENZALKONIUM CHLORIDE 130 mg/100 mL
INACTIVE INGREDIENTS: METHYLCHLOROISOTHIAZOLINONE; METHYLISOTHIAZOLINONE; SODIUM SULFATE; GLYCERIN; COCO MONOETHANOLAMIDE; PEG-120 METHYL GLUCOSE DIOLEATE; CITRIC ACID MONOHYDRATE; FD&C RED NO. 40; BASIC YELLOW 5; EDETATE SODIUM; D&C RED NO. 33; WATER; CETRIMONIUM CHLORIDE; SODIUM CHLORIDE; LAURAMIDOPROPYLAMINE OXIDE; FRAGRANCE CLEAN ORC0600327

CVS, 51316-703

Purpose

Antibacterial

ACTIVE INGREDIENT

Benzalkonium Chloride.

WARNINGS

For External Use only

KEEP OUT OF REACH OF CHILDREN

In case of accidental ingestion, seek medical attention or contact a poison control centre immediately

ask a doctor ifIrritation or redness develops and lasts

DOSAGE AND ADMINISTRATION

Apply onto dry hands. Work into a lather, rinse and dry throughly.

STORAGE AND HANDLING

Store at room temperature

INACTIVE INGREDIENT

Water (aqua), Lauramidopropylamine oxide, Glycerin, Cetrimonium Chloride, Sodium Chloride, Cocamide MEA, PEG-120 Methyl Glucose Dioleate, Fragrance (Parfum), Citric Acid, Tetrasodium EDTA, Sodium Sulfate, Methylchloroisothiazolinone, Methylisothiazolinone, Red 40 (Cl16035), Yellow 5 (Cl 19140), Red 33 (Cl 17200)

INDICATIONS AND USAGE

Helps eliminate bacteria on skin